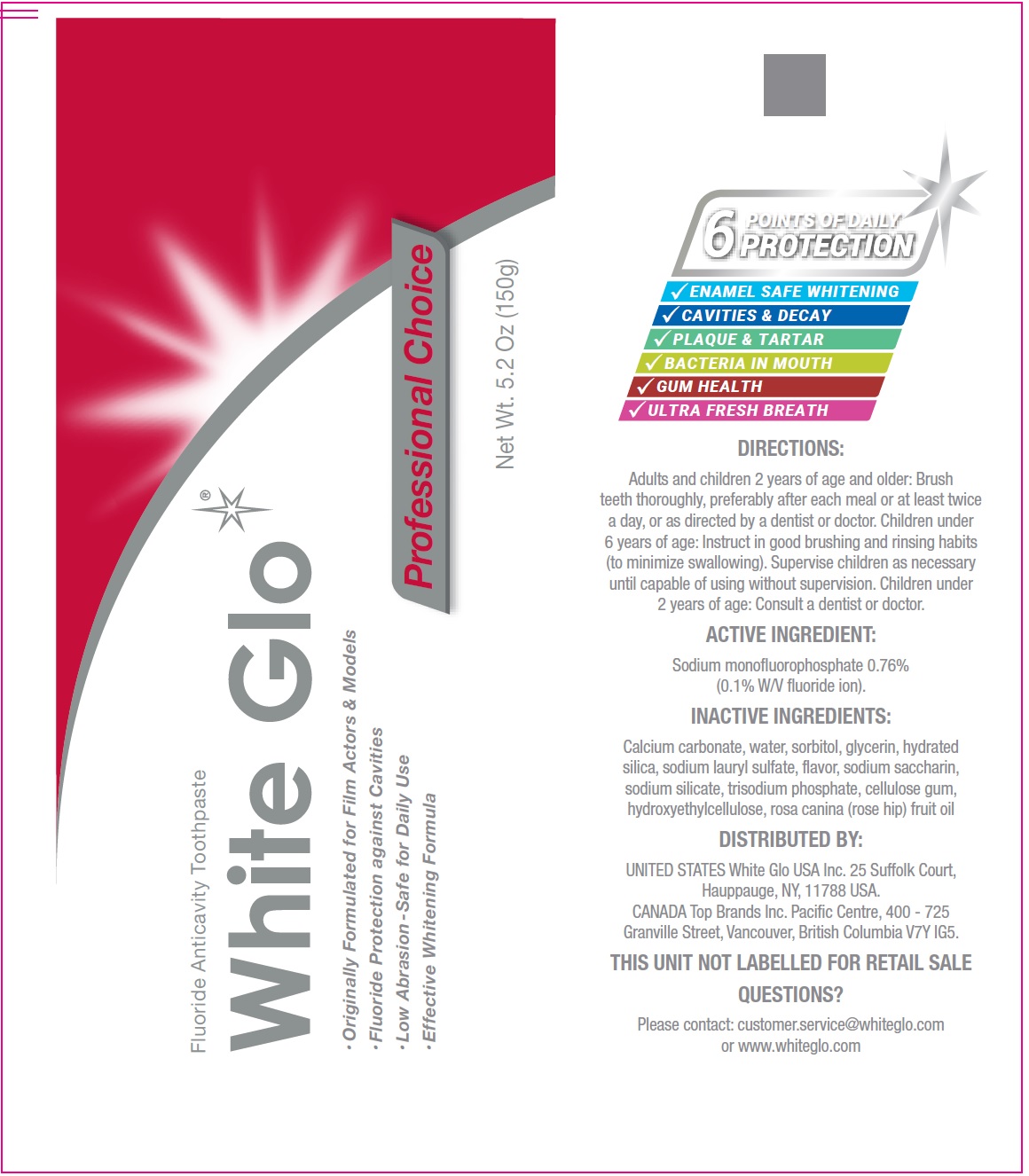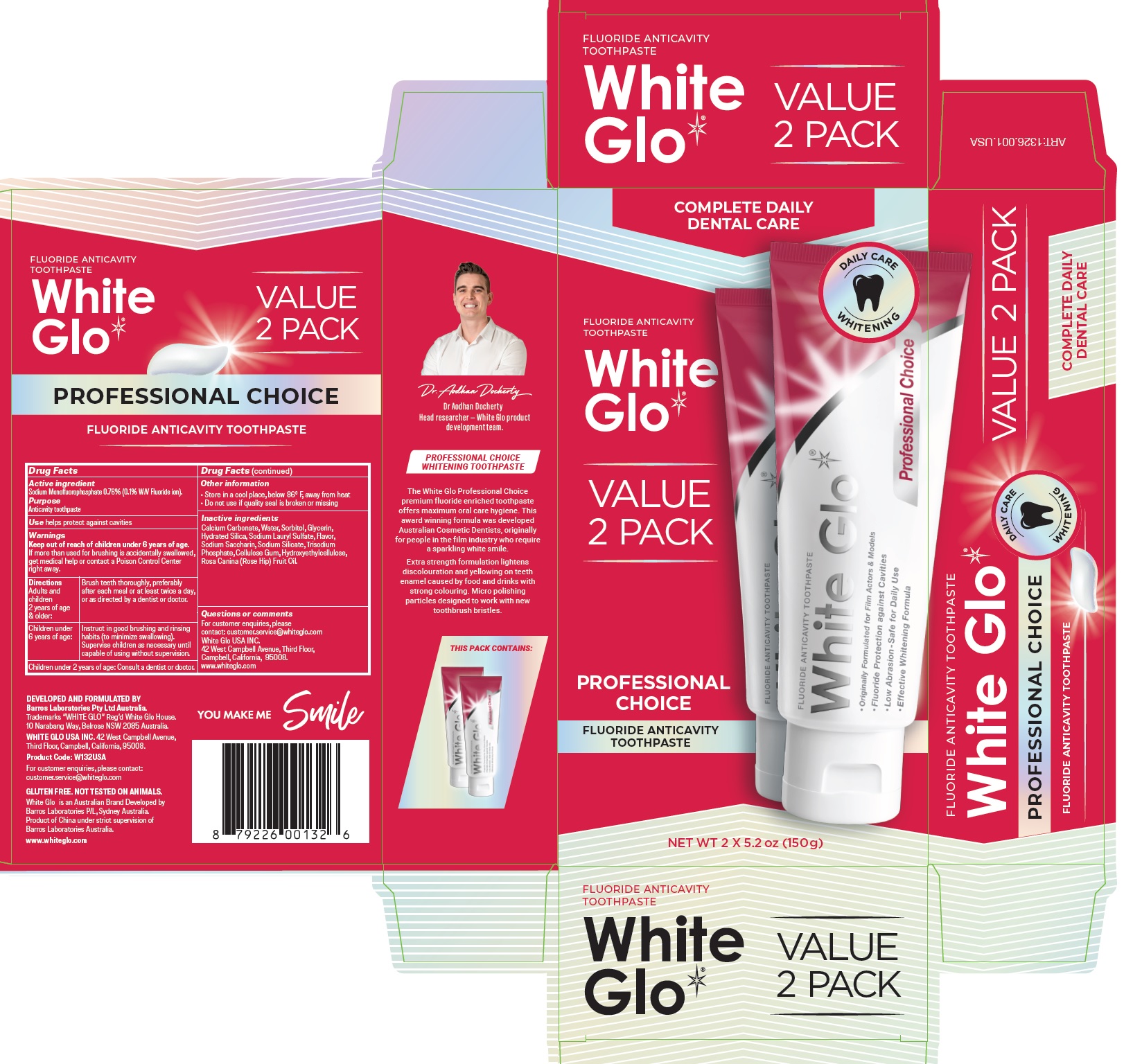 DRUG LABEL: White Glo Professional Choice Fluoride Anticavity
NDC: 73656-043 | Form: PASTE, DENTIFRICE
Manufacturer: White Glo USA Inc
Category: otc | Type: HUMAN OTC DRUG LABEL
Date: 20260219

ACTIVE INGREDIENTS: SODIUM MONOFLUOROPHOSPHATE 7.6 mg/1 g
INACTIVE INGREDIENTS: CALCIUM CARBONATE; WATER; SORBITOL; GLYCERIN; HYDRATED SILICA; SODIUM LAURYL SULFATE; SACCHARIN SODIUM; SODIUM SILICATE; CARBOXYMETHYLCELLULOSE SODIUM, UNSPECIFIED; HYDROXYETHYL CELLULOSE, UNSPECIFIED; ROSA CANINA FRUIT OIL

White Glo Professional Choice Fluoride Anticavity Toothpaste

Active ingredient

Sodium Monofluorophosphate 0.76% (0.1% W/V Fluoride ion).

Purpose

Anticavity toothpaste

Use

helps protect against cavities

Warnings

Keep out of reach of children under 6 years of age.

If more than used for brushing is accidentally swallowed, get medical help or contact a Poison Control Center right away.

Directions

Adults and children 2 years of age & older: | Brush teeth thoroughly, preferably after each meal or at least twice a day, or as directed by a dentist or doctor.
Children under 6 years of age: | Instruct in good brushing and rinsing habits (to minimize swallowing). Supervise children as necessary until capable of using without supervision.

Children under 2 years of age: Consult a dentist or doctor.

Other information

• Store in a cool place, below 86 F, away from heat
• Do not use if quality seal is broken or missing

Inactive ingredients

Calcium Carbonate, Water, Sorbitol, Glycerin, Hydrated Silica, Sodium Lauryl Sulfate, Flavor, Sodium Saccharin, Sodium Silicate, Trisodium Phosphate, Cellulose Gum, Hydroxyethylcellulose, Rosa Canina (Rose Hip) Fruit Oil.

Questions or comments

For customer enquiries, please contact: customer.service@whiteglo.com
White Glo USA INC. 42 West Campbell Avenue, Third Floor, Campbell, California, 95008.
www.whiteglo.com